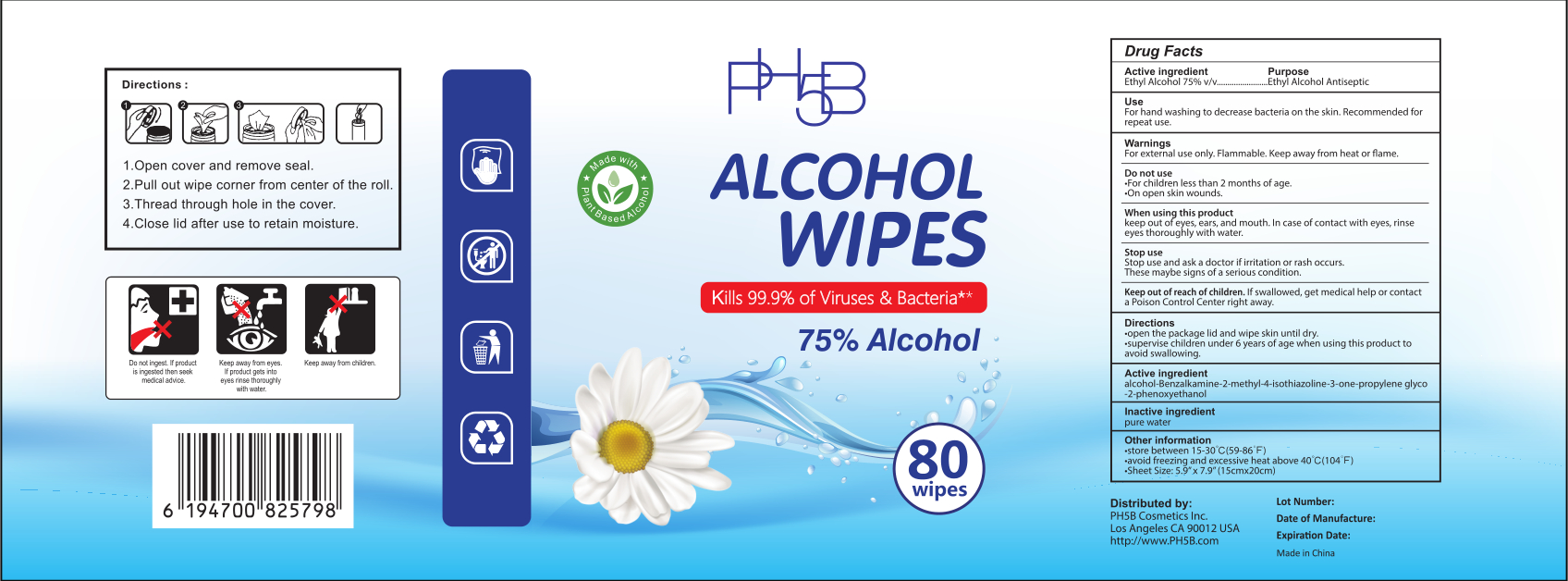 DRUG LABEL: ALCOHOL  WIPES
NDC: 41546-022 | Form: CLOTH
Manufacturer: Zhejiang Huanghua Biological Technology Co., Ltd
Category: otc | Type: HUMAN OTC DRUG LABEL
Date: 20201222

ACTIVE INGREDIENTS: ALCOHOL 75 g/100 g; BENZALKONIUM CHLORIDE 0.6 g/100 g; METHYLISOTHIAZOLINONE 0.6 g/100 g; PROPYLENE GLYCOL 0.6 g/100 g; PHENOXYETHANOL 0.6 g/100 g
INACTIVE INGREDIENTS: WATER

DOSAGE AND ADMINISTRATION

store between 15-30°C(59-86°F),avoid freezing and excessive heat above 40°C(104°F)

INACTIVE INGREDIENT

pure water

INDICATIONS AND USAGE

1.Open cover and remove seal.
2.Pull out wipe corner from center of the roll.
3.Thread through hole in the cover.
4.Close lid after use to retain moisture.

ACTIVE INGREDIENT

alcohol

Benzalkamine

2-methyl-4-isothiazoline-3-one

propylene glyco

2-phenoxyethanol

Stop use and ask a doctor if irritation or rash occurs.These maybe signs of a serious condition.

Keep out of reach of children. If swallowed, get medical help or contacta Poison Control Center right away.

PURPOSE

Disinfection
Sterilization
No Rinseing

WARNINGS

For external use only. Flammable. Keep away from heat or flame.